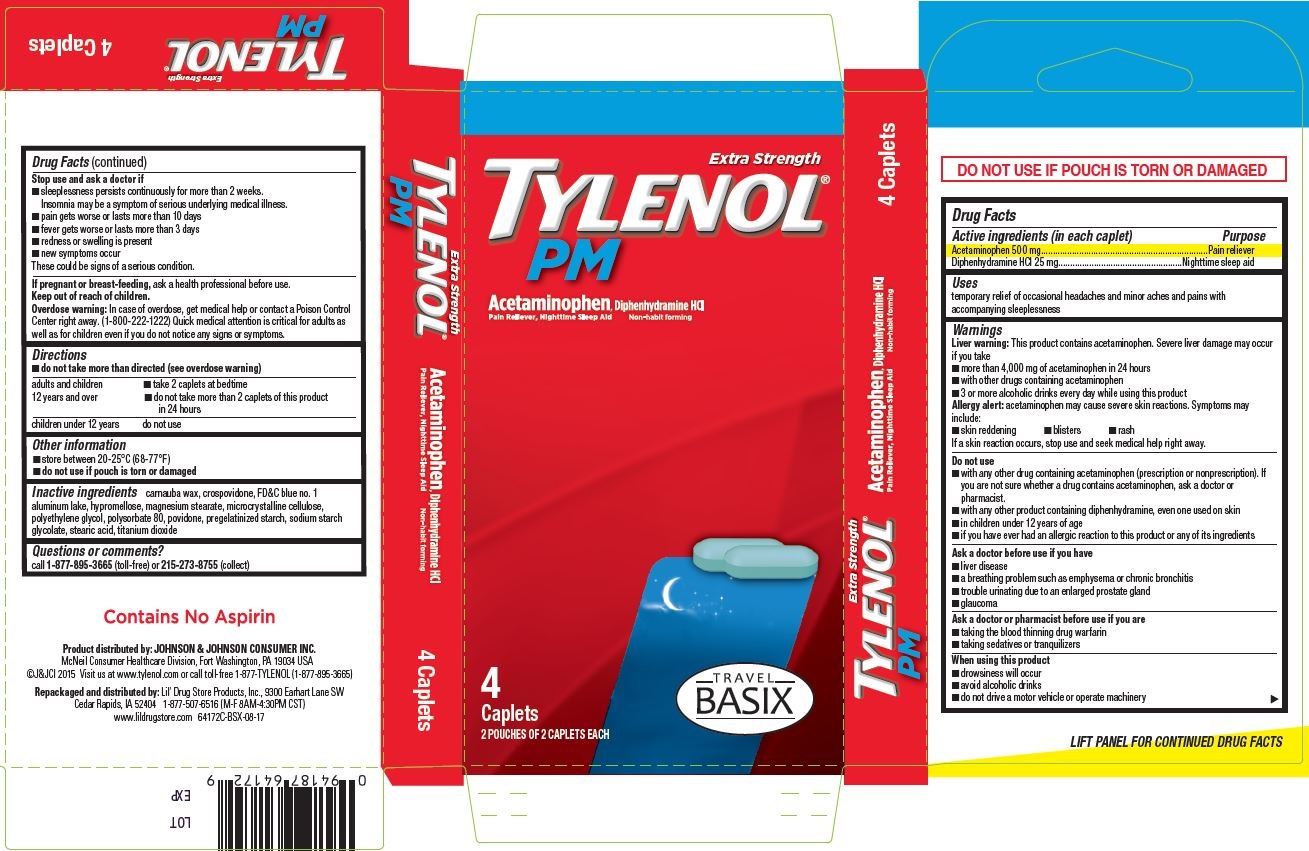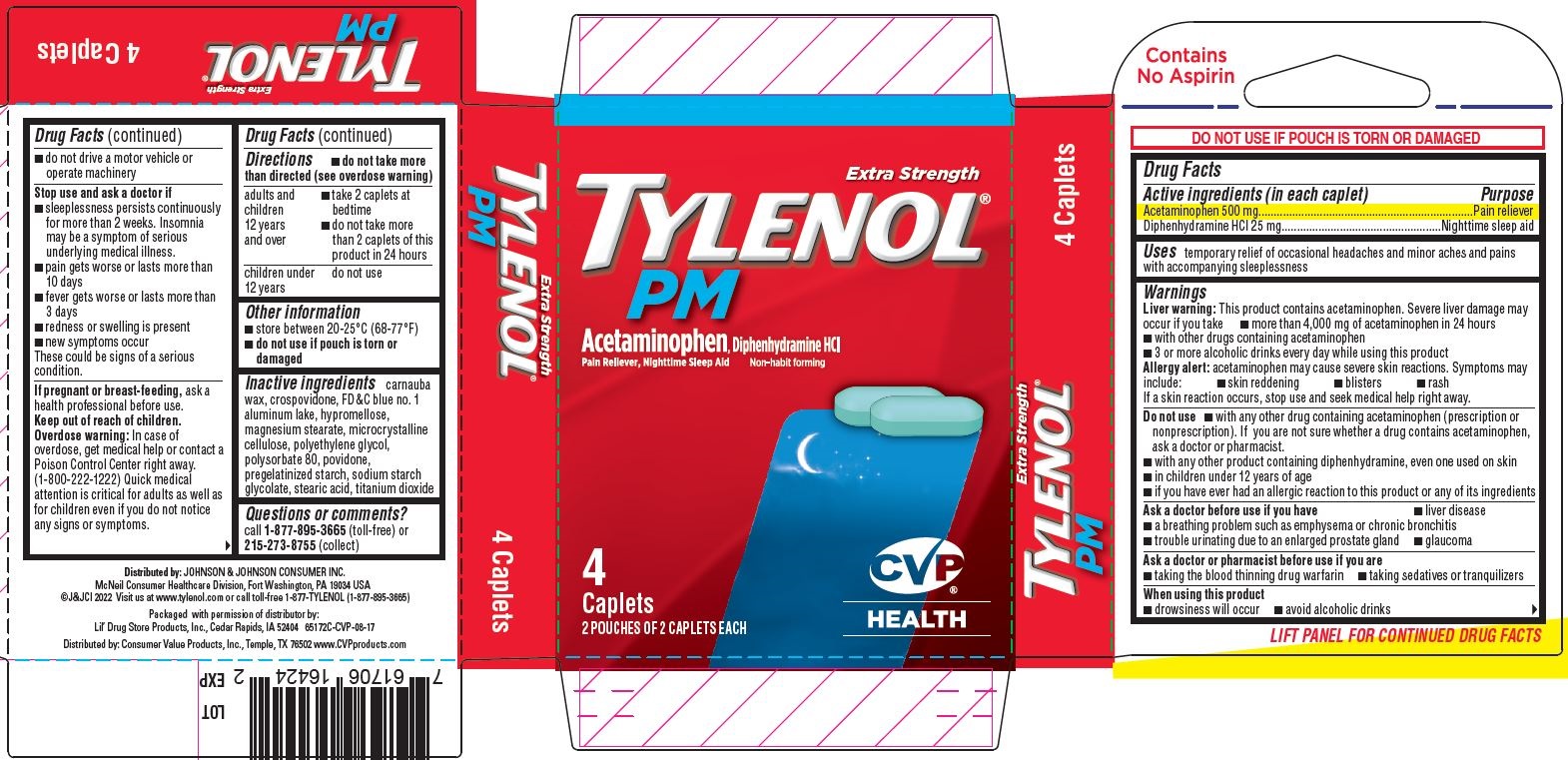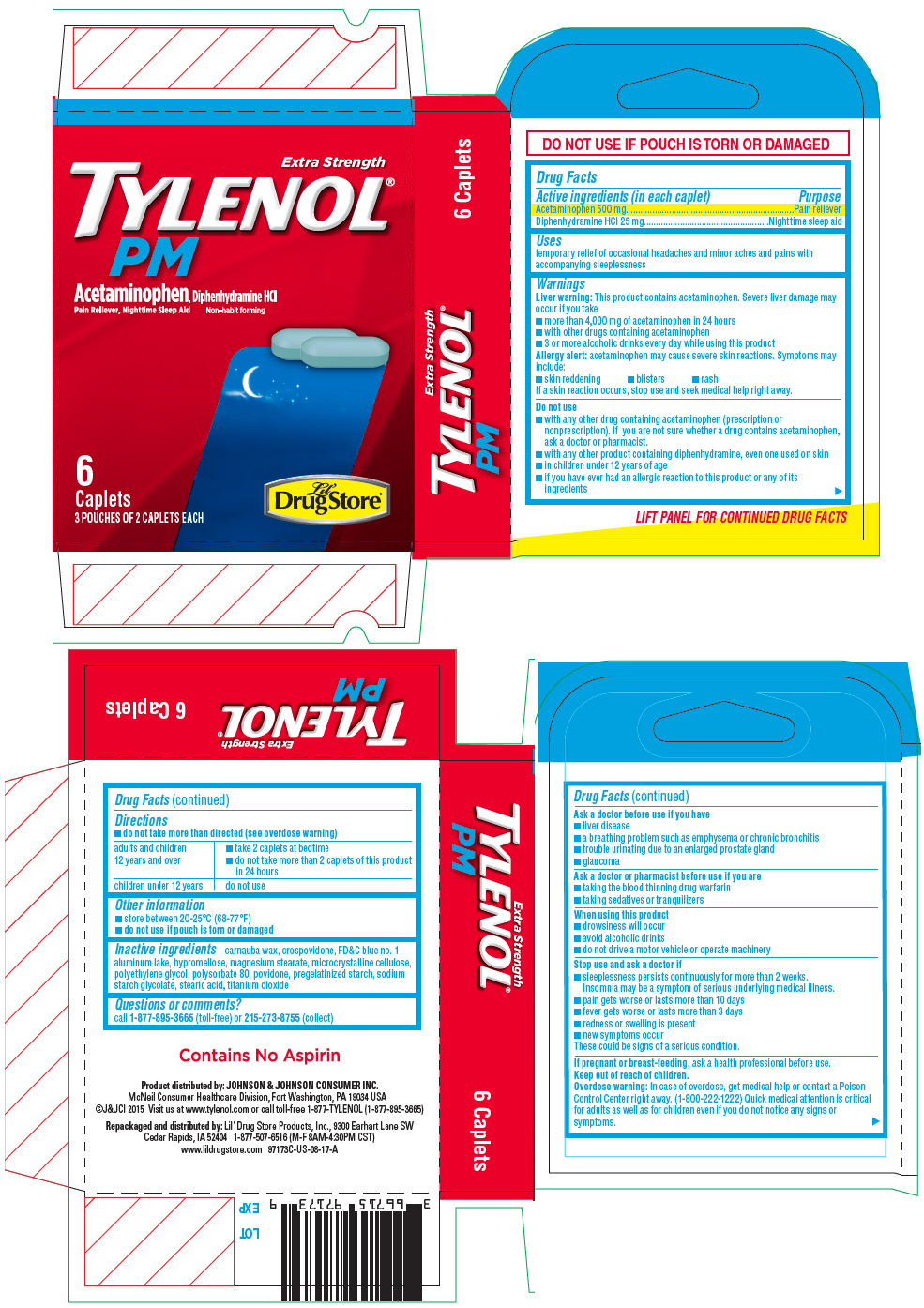 DRUG LABEL: Lil Drug Store Tylenol PM Extra Strength
NDC: 66715-9817 | Form: TABLET, FILM COATED
Manufacturer: Lil' Drug Store Products, Inc.
Category: otc | Type: HUMAN OTC DRUG LABEL
Date: 20251210

ACTIVE INGREDIENTS: DIPHENHYDRAMINE HYDROCHLORIDE 25 mg/1 1; ACETAMINOPHEN 500 mg/1 1
INACTIVE INGREDIENTS: CARNAUBA WAX; CROSPOVIDONE (15 MPA.S AT 5%); FD&C BLUE NO. 1; ALUMINUM OXIDE; HYPROMELLOSE, UNSPECIFIED; MICROCRYSTALLINE CELLULOSE; POLYETHYLENE GLYCOL, UNSPECIFIED; POLYSORBATE 80; MAGNESIUM STEARATE; POVIDONE, UNSPECIFIED; STARCH, CORN; SODIUM STARCH GLYCOLATE TYPE A POTATO; STEARIC ACID; TITANIUM DIOXIDE

Tylenol® PM Extra Strength,
Lil' Drug Store®, CVP® HEALTH, Travel BASIX

Drug Facts

ACTIVE INGREDIENT

Active ingredients (in each caplet) | Purpose
Acetaminophen 500 mg | Pain reliever
Diphenhydramine HCl 25 mg | Nighttime sleep aid

Uses

temporary relief of occasional headaches and minor aches and pains with accompanying sleeplessness

Warnings

Liver warning

This product contains acetaminophen. Severe liver damage may occur if you take

- more than 4,000 mg of acetaminophen in 24 hours
- with other drugs containing acetaminophen
- 3 or more alcoholic drinks every day while using this product

Allergy alert: acetaminophen may cause severe skin reactions. Symptoms may include:

- skin reddening
- blisters
- rash

If a skin reaction occurs, stop use and seek medical help right away.

Do not use

- with any other drug containing acetaminophen (prescription or nonprescription). If you are not sure whether a drug contains acetaminophen, ask a doctor or pharmacist.
- with any other product containing diphenhydramine, even one used on skin
- in children under 12 years of age
- if you have ever had an allergic reaction to this product or any of its ingredients

Ask a doctor before use if you have

- liver disease
- a breathing problem such as emphysema or chronic bronchitis
- trouble urinating due to an enlarged prostate gland
- glaucoma

Ask a doctor or pharmacist before use if you are

- taking the blood thinning drug warfarin
- taking sedatives or tranquilizers

When using this product

- drowsiness will occur
- avoid alcoholic drinks
- do not drive a motor vehicle or operate machinery

Stop use and ask a doctor if

- sleeplessness persists continuously for more than 2 weeks. Insomnia may be a symptom of serious underlying medical illness.
- pain gets worse or lasts more than 10 days
- fever gets worse or lasts more than 3 days
- redness or swelling is present
- new symptoms occur

These could be signs of a serious condition.

PREGNANCY OR BREAST FEEDING

If pregnant or breast-feeding, ask a health professional before use.

Keep out of reach of children.

Overdose warning

In case of overdose, get medical help or contact a Poison Control Center right away. (1-800-222-1222) Quick medical attention is critical for adults as well as for children even if you do not notice any signs or symptoms.

Directions

- do not take more than directed (see overdose warning)

adults and children 12 years and over | - take 2 caplets at bedtime - do not take more than 2 caplets of this product in 24 hours
children under 12 years | do not use

Other information

- store between 20-25°C (68-77°F)
- do not use if pouch is torn or damaged

Inactive ingredients

carnauba wax, crospovidone, FD&C blue no. 1 aluminum lake, hypromellose, magnesium stearate, microcrystalline cellulose, polyethylene glycol, polysorbate 80, povidone, pregelatinized starch, sodium starch glycolate, stearic acid, titanium dioxide

Questions or comments?

call 1-877-895-3665 (toll-free) or 215-273-8755 (collect)

Product distributed by: JOHNSON & JOHNSON CONSUMER INC.
McNeil Consumer Healthcare Division, Fort Washington, PA 19034 USA

Repackaged and distributed by: Lil' Drug Store Products, Inc., 9300 Earhart Lane SW
Cedar Rapids, IA 52402

PRINCIPAL DISPLAY PANEL - 6 Caplet Pouch Carton

Extra Strength
TYLENOL®
PM

Acetaminophen, Diphenhydramine HCl
Pain Reliever, Nighttime Sleep Aid
Non-habit forming

6
Caplets
3 POUCHES OF 2 CAPLETS EACH

Lil'
DrugStore®

Extra Strength Tylenol® PM, CVP® HEALTH, 4ct - PDP/Package

Extra Strength
TYLENOL®
PM

Acetaminophen, Diphenhydramine HCl
Pain Reliever, Nighttime Sleep Aid
Non-habit forming

[caplets image]

4
Caplets
2 POUCHES OF 2 CAPLETS EACH

[CVP® HEALTH logo]

Tylenol® PM Extra Strength, Travel BASIX

Extra Strength
TYLENOL®
PM

Acetaminophen, Diphenhydramine HCl
Pain Reliever, Nighttime Sleep Aid Non-habit forming

[caplets image]

4
Caplets
2 POUCHES OF 2 CAPLETS EACH

[Travel BASIX logo]